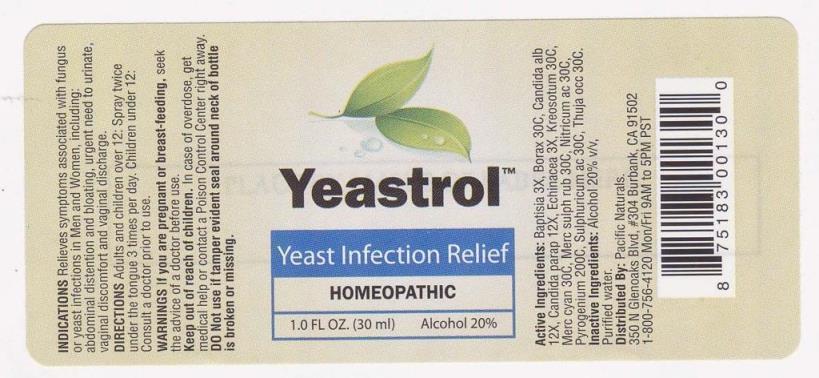 DRUG LABEL: Yeastrol
NDC: 43695-0006 | Form: SPRAY
Manufacturer: Pacific Naturals
Category: homeopathic | Type: HUMAN OTC DRUG LABEL
Date: 20150318

ACTIVE INGREDIENTS: BAPTISIA TINCTORIA ROOT 3 [hp_X]/1 mL; SODIUM BORATE 30 [hp_C]/1 mL; CANDIDA ALBICANS 12 [hp_X]/1 mL; CANDIDA PARAPSILOSIS 12 [hp_X]/1 mL; ECHINACEA ANGUSTIFOLIA 3 [hp_X]/1 mL; WOOD CREOSOTE 30 [hp_C]/1 mL; MERCURIC CYANIDE 30 [hp_C]/1 mL; MERCURIC SULFIDE 30 [hp_C]/1 mL; NITRIC ACID 30 [hp_C]/1 mL; RANCID BEEF 200 [hp_C]/1 mL; SULFURIC ACID 30 [hp_C]/1 mL; THUJA OCCIDENTALIS LEAFY TWIG 30 [hp_C]/1 mL
INACTIVE INGREDIENTS: WATER; ALCOHOL

DRUG FACTS:

ACTIVE INGREDIENTS:

Baptisia Tinctoria 3X, Borax 30C, Candida Albicans 12X, Candida Parapsilosis 12X, Echinacea (Angustifolia) 3X, Kreosotum 30C, Mercurius Cyanatus 30C, Mercurius Sulphuratus Ruber 30C, Nitricum Acidum 30C, Pyrogenium 200C, Sulphuricum Acidum 30C, Thuja Occidentalis 30C

INDICATIONS:

Relieves symptoms associated with fungus or yeast infections in Men and Women, including: abdominal distention and bloating, urgent need to urinate, vaginal discomfort and vaginal discharge.

WARNINGS:

If you are pregnant or breast-feeding, seek the advice of a doctor before use.

Keep out of reach of children. In case of overdose, get medical help or contact a Poison Control Center right away.

DO not use if tamper evident seal around neck of bottle is broken or missing.

Keep out of reach of children. In case of overdose, get medical help or contact a Poison Control Center right away.

DIRECTIONS:

Adults and children over 12: Spray twice under the tongue three times per day.

Children under 12: Consult a doctor prior to use.

INDICATIONS:

Relieves symptoms associated with fungus or yeast infections in Men and Women, including: abdominal distention and bloating, urgent need to urinate, vaginal discomfort and vaginal discharge.

INACTIVE INGREDIENTS:

Alcohol 20% v/v, Purified water

QUESTIONS:

Distributed By: Pacific Naturals.

350 N Glenoaks Blvd, #304 Burbank, CA 91502

1-800-756-4120 Mon/Fri 9AM to 5 PM PST

PACKAGE LABEL DISPLAY:

Yeastrol

Yeast Infection Relief

Homeopathic

1.0 FL OZ. (30 ml)